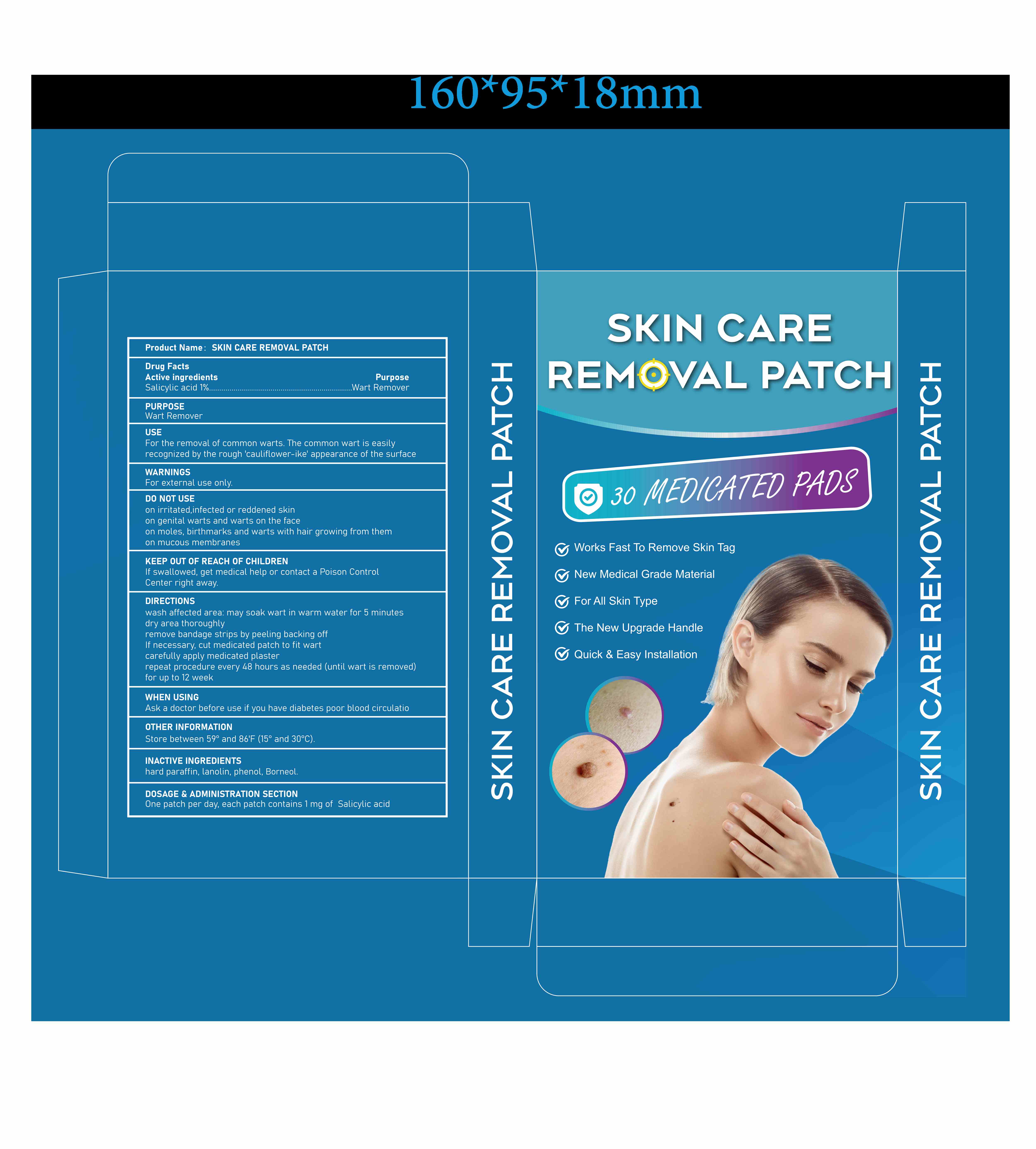 DRUG LABEL: SKIN CARE REMOVAL
NDC: 84023-114 | Form: PATCH
Manufacturer: Shenzhen Yangan Technology Co., Ltd.
Category: otc | Type: HUMAN OTC DRUG LABEL
Date: 20241230

ACTIVE INGREDIENTS: SALICYLIC ACID 1 mg/100 mg
INACTIVE INGREDIENTS: LANOLIN; PARAFFIN; BORNEOL; PHENOL

SKIN CARE REMOVAL PATCH

ACTIVE INGREDIENT

Salicylic acid 1%

PURPOSE

Wart Remover

WARNINGS

For external use only.

DO NOT USE

on irritated, infected or reddened skin

on genital warts and warts on the face

on moles, birthmarks and warts with hair growing from them

on mucous membranes

KEEP OUT OF REACH OF CHILDREN

If swallowed, get medical help or contact a Poison Control

Center right away.

WHEN USING

Ask a doctor before use if you have diabetes poor blood circulation

DOSAGE & ADMINISTRATION SECTION

One patch per day, each patch contains 1 mg of Salicylic acid

USE

For the removal of common warts. The common wart is easily

recognized by the rough 'cauliflower-ike' appearance of the surface

OTHER INFORMATION

Store between 59°and 86'F (15°and 30°C).

INACTIVE INGREDIENT

hard paraffin, lanolin,phenol, Borneol.